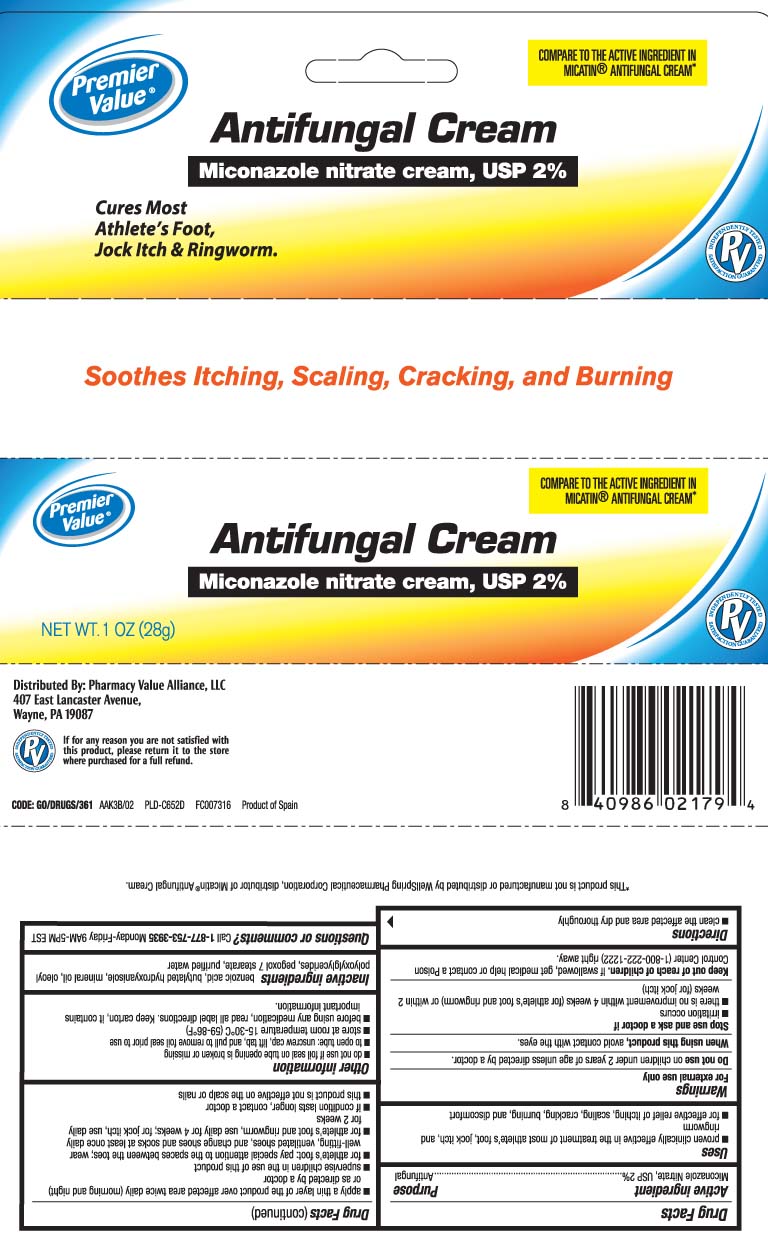 DRUG LABEL: Miconazole
NDC: 68016-291 | Form: CREAM
Manufacturer: Chain Drug Consortium, LLC
Category: otc | Type: HUMAN OTC DRUG LABEL
Date: 20250630

ACTIVE INGREDIENTS: MICONAZOLE NITRATE 20 mg/1 g
INACTIVE INGREDIENTS: BENZOIC ACID; BUTYLATED HYDROXYANISOLE; MINERAL OIL; PEGOXOL 7 STEARATE; WATER

Miconazole Nitrate Cream, USP

Active ingredient

Miconazole nitrate, USP 2%

Purpose

Antifungal

Uses

- proven clinically effective in the treatment of most athlete's foot, jock itch, and ringworm
- for effective relief of itching, scaling, cracking, burning, and discomfort

Warnings

For external use only

Do not use

on children under 2 years of age unless directed by a doctor.

When using this product

- avoid contact with the eyes

Stop use and ask a doctor if

- irritation occurs
- there is no improvement within 4 weeks (for athlete's foot and ringworm) or within 2 weeks (for jock itch)

Keep out of reach of children.

If swallowed, get medical help or contact a Poison Control Center (1-800-222-1222) right away.

Directions

- clean the affected area and dry thoroughly
- apply a thin layer of the product over affected area twice daily (morning and night), or as directed by a doctor
- supervise children in the use of this product
- for athlete's foot: pay special attention to spaces between the toes; wear well-fitting, ventilated shoes, and change shoes and socks at least once daily
- for athlete's foot and ringworm, use daily for 4 weeks; for jock itch, use daily for 2 weeks
- if condition lasts longer, contact a doctor
- this product is not effective on the scalp or nails

Other information

- do not use if foil seal on tube opening is broken or missing
- to open tube: unscrew cap, lift tab, and pull to remove foil seal prior to use
- store at room temperature 15-30°C (59-86°F)
- before using any medication, read all label directions. Keep carton, it contains important information.

Inactive ingredients

benzoic acid, butylated hydroxyanisole, mineral oil, oleoyl polyoxylglycerides, pegoxol 7 stearate, purified water

Questions or comments?

Call 1-877-753-3935 Monday-Friday 9AM-5PM EST

Principal display panel

COMPARE TO THE ACTIVE INGREDIENT IN MICARIN® ANTIFUNGAL CREAM*

Antifungal Cream

Miconazole nitrate cream, USP 2%

Cures Most

Athlete's Foot,

Jock Itch & Ringworm.

Soothes Itching, Scaling, Cracking, and Burning

*This product is not manufactured or distributed by WellSpring Pharmaceutical Corporation, distributor of Micatin® Antifungal Cream.

Distributed By: Pharmacy Value Alliance, LLC

407 East Lancaster Avenue,

Wayne, PA 19087

Package label

PREMIER VALUE Antifungal Cream